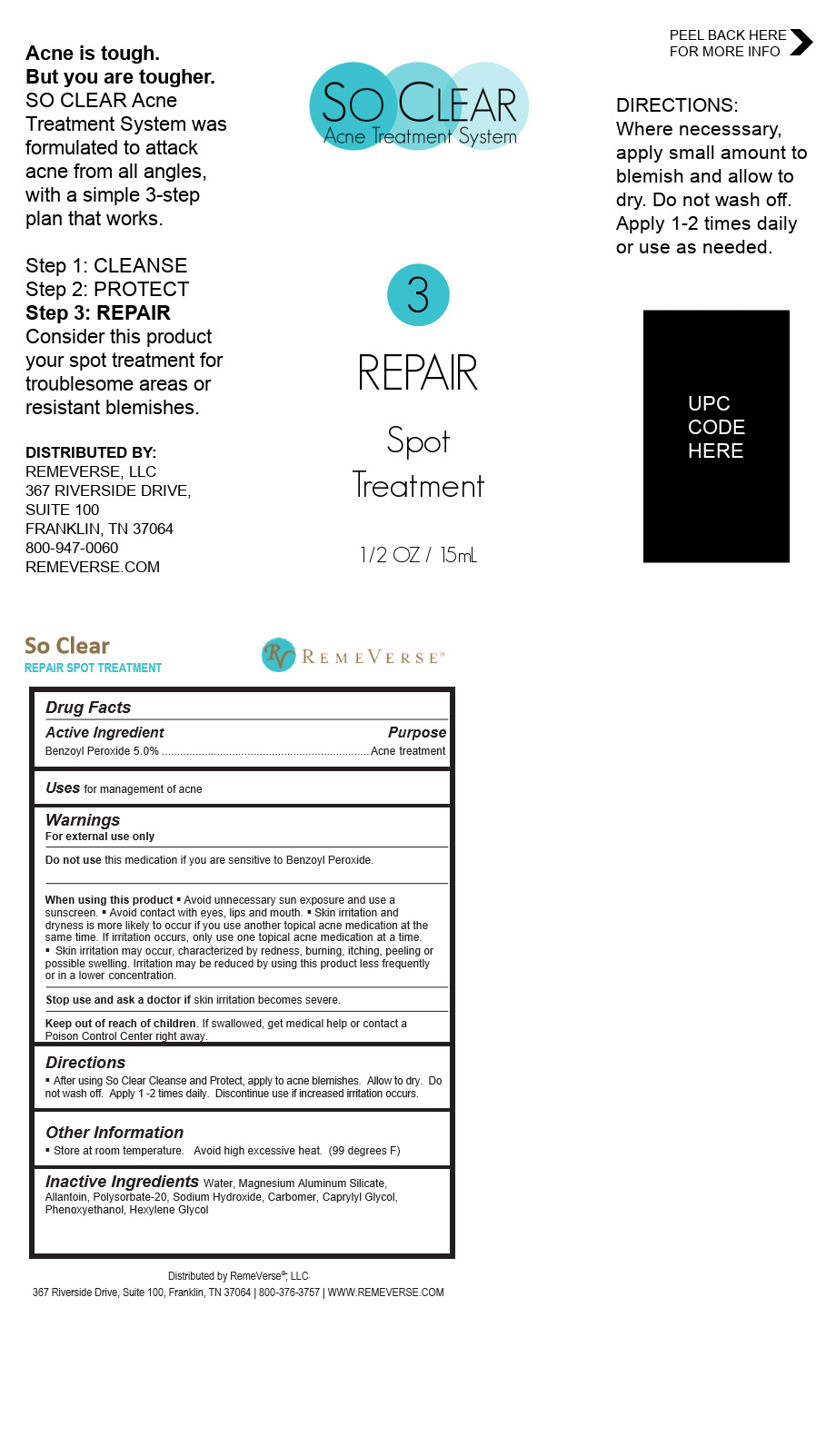 DRUG LABEL: So Clear Repair Spot Treatment
NDC: 70317-148 | Form: LIQUID
Manufacturer: RemeVerse LLC
Category: otc | Type: HUMAN OTC DRUG LABEL
Date: 20241216

ACTIVE INGREDIENTS: BENZOYL PEROXIDE 0.7875 g/15 mL
INACTIVE INGREDIENTS: POLYSORBATE 20; HEXYLENE GLYCOL; CARBOMER 940; ALLANTOIN; OCTYLPHENOXYETHANOL; CAPRYLYL GLYCOL; SODIUM HYDROXIDE

So Clear Repair Spot Treatment

So Clear Repair Spot Treatment

Benzoyl Peroxide 5.0%

So Clear Repair Spot Treatment

Water, Magnesium Aluminum Silicate, Allantoin, Polysorbate-20, Sodium Hydroxide, Carbomer, Caprylyl Glycol, Phenoxyethanol, Hexylene Glycol

Directions

After using So Clear Cleanse and Protect, apply to acne blemishes. Allow to dry. Do not wash off. Apply 1 -2 times daily. Discontinue use if increased irritation occurs.

Uses

for management of acne

Store at room temperature. Avoid high excessive heat. (99 degrees F)

Warnings

For external use only

Do not use this medication if you are sensitive to Benzoyl Peroxide.

When using this product § Avoid unnecessary sun exposure and use a sunscreen. § Avoid contact with eyes, lips and mouth. § Skin irritation and dryness is more likely to occur if you use another topical acne medication at the same time. If irritation occurs, only use one topical acne medication at a time.

Skin irritation may occur, characterized by redness, burning, itching, peeling or possible swelling. Irritation may be reduced by using this product less frequently or in a lower concentration.

Stop use and ask a doctor if skin irritation become severe

Keep out of the reach of children If swallowed, get medical help or contact a Poison Control Center right away.

Stop use and ask a doctor if skin irritation becomes severe.

PURPOSE

Acne treatment

Other Information

Store at room temperature. Avoid high excessive heat. (99 degrees F)

Keep out of the reach of children

If swallowed, get medical help or contact a Poison Control Center right away